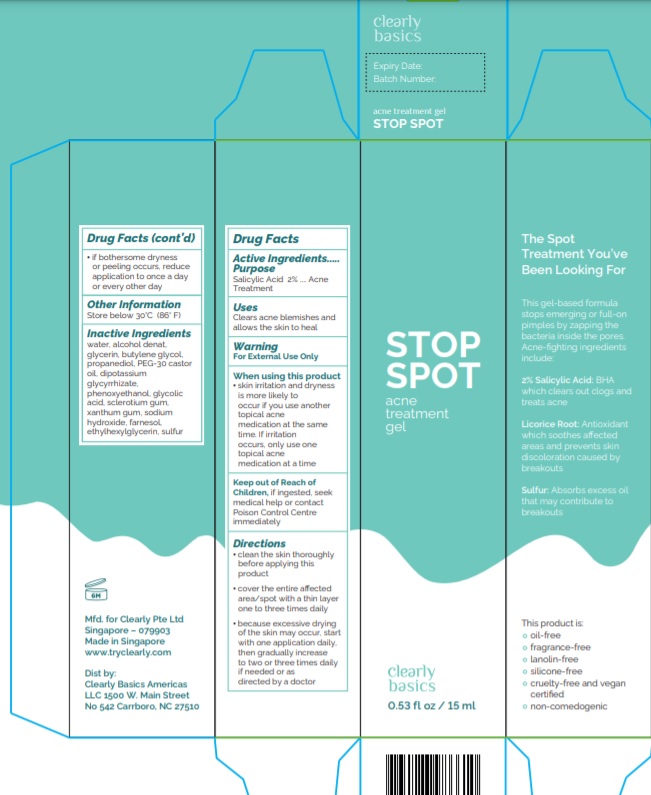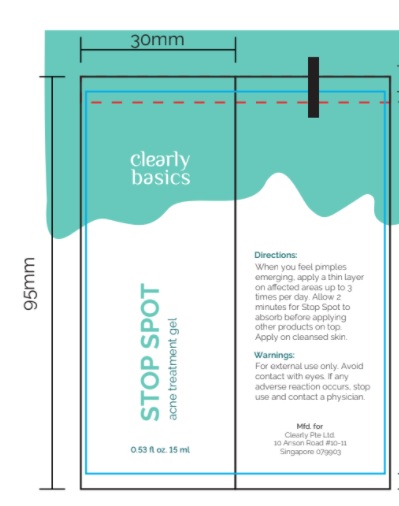 DRUG LABEL: STOP SPOT
NDC: 72521-001 | Form: GEL
Manufacturer: Clearly Pte Ltd
Category: otc | Type: HUMAN OTC DRUG LABEL
Date: 20230113

ACTIVE INGREDIENTS: SALICYLIC ACID 2 g/100 mL
INACTIVE INGREDIENTS: WATER; ALCOHOL; GLYCERIN; BUTYLENE GLYCOL; PROPANEDIOL; PEG-30 CASTOR OIL; GLYCYRRHIZINATE DIPOTASSIUM; PHENOXYETHANOL; GLYCOLIC ACID; BETASIZOFIRAN; XANTHAN GUM; SODIUM HYDROXIDE; FARNESOL; ETHYLHEXYLGLYCERIN; SULFUR

Active ingredient

Salicylic Acid 2%

Purpose

Acne treatment

Uses

Clears acne blemishes and allows the skin to heal

Warnings

For External Use Only

When using this product skin irritation and dryness is more likely to occur if you use another topical acne medication at the same time. If irritation occurs, only use one topical acne medication at a time

Keep out of Reach of Children, if ingested, seek medical help or contact Poison
Control Center immediately

Directions

- Clean the skin thoroughly before applying this product
- cover the entire affected area/spot with a thin layer one to three times daily
- because excessive drying of the skin may occur, start with one application daily, then gradually increase to two or three times daily if needed or as directed by a doctor

- if bothersome dryness or peeling occurs, reduce application to once a day or every other day

Other information

Store below 30°C (86° F)

Inactive ingredients

water, alcohol denat, glycerin, butylene glycol, propanediol, PEG-30 castor oil, dipotassium glycyrrhizate, phenoxyethanol, glycolic acid, sclerotium gum,xanthum gum, sodium hydroxide, farnesol, ethylhexylglycerin, sulfur